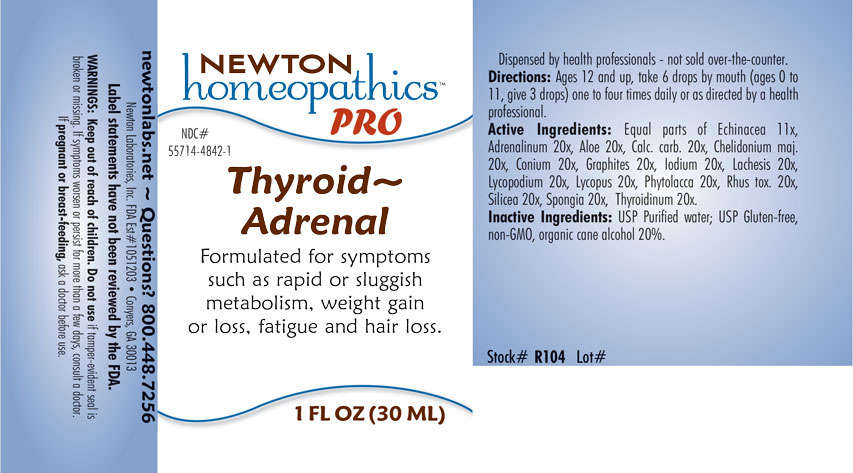 DRUG LABEL: Thyroid-Adrenal
NDC: 55714-4842 | Form: LIQUID
Manufacturer: Newton Laboratories, Inc.
Category: homeopathic | Type: HUMAN OTC DRUG LABEL
Date: 20201201

ACTIVE INGREDIENTS: EPINEPHRINE 20 [hp_X]/1 mL; THYROID, UNSPECIFIED 20 [hp_X]/1 mL; ALOE 20 [hp_X]/1 mL; OYSTER SHELL CALCIUM CARBONATE, CRUDE 20 [hp_X]/1 mL; CHELIDONIUM MAJUS 20 [hp_X]/1 mL; CONIUM MACULATUM FLOWERING TOP 20 [hp_X]/1 mL; GRAPHITE 20 [hp_X]/1 mL; IODINE 20 [hp_X]/1 mL; LACHESIS MUTA VENOM 20 [hp_X]/1 mL; LYCOPODIUM CLAVATUM SPORE 20 [hp_X]/1 mL; LYCOPUS VIRGINICUS 20 [hp_X]/1 mL; PHYTOLACCA AMERICANA ROOT 20 [hp_X]/1 mL; TOXICODENDRON PUBESCENS LEAF 20 [hp_X]/1 mL; SILICON DIOXIDE 20 [hp_X]/1 mL; SPONGIA OFFICINALIS SKELETON, ROASTED 20 [hp_X]/1 mL; ECHINACEA, UNSPECIFIED 11 [hp_X]/1 mL
INACTIVE INGREDIENTS: WATER; ALCOHOL

Thyroid 4842L

OTC - KEEP OUT OF REACH OF CHILDREN SECTION

Keep out of reach of children.

OTC - PREGNANCY OR BREAST FEEDING SECTION

If pregnant or breast-feeding, ask a doctor before use.

WARNINGS SECTION

WARNINGS: Keep out of reach of children. Do not use if tamper-evident seal is broken or missing. If symptoms worsen or persist for more than a few days, consult a doctor. If pregnant or breast-feeding, ask a doctor before use.

QUESTIONS SECTION

Newtonlabs.net - Questions? 1.800.448.7256

Newton Laboratories, Inc. FDA Est # 1051203 - Conyers, GA 30013

INACTIVE INGREDIENT SECTION

Inactive Ingredients: USP Purified Water; USP Gluten-free, non-GMO, organic cane alcohol 20%.

OTC - PURPOSE SECTION

Formulated for symptoms such as rapid or sluggish metabolism, weight gain or loss, fatigue and hair loss.

OTC - ACTIVE INGREDIENT SECTION

Equal parts of Echinacea 11x, Adrenalinum 20x, Aloe 20x, Calcarea carbonica 20x, Chelidonium majus 20x, Conium maculatum 20x, Graphites 20x, Iodium 20x, Lachesis mutus 20x, Lycopodium clavatum 20x, Lycopus virginicus 20x, Phytolacca decandra 20x, Rhus toxicodendron 20x, Silicea 20x, Spongia tosta 20x, Thyroidinum 20x.

DOSAGE & ADMINISTRATION SECTION

Directions: Ages 12 and up, take 6 drops by mouth (ages 0 to 11, give 3 drops) one to four times daily or as directed by a health professional.

INDICATIONS & USAGE SECTION

Formulated for symptoms such as rapid or sluggish metabolism, weight gain or loss, fatigue and hair loss.